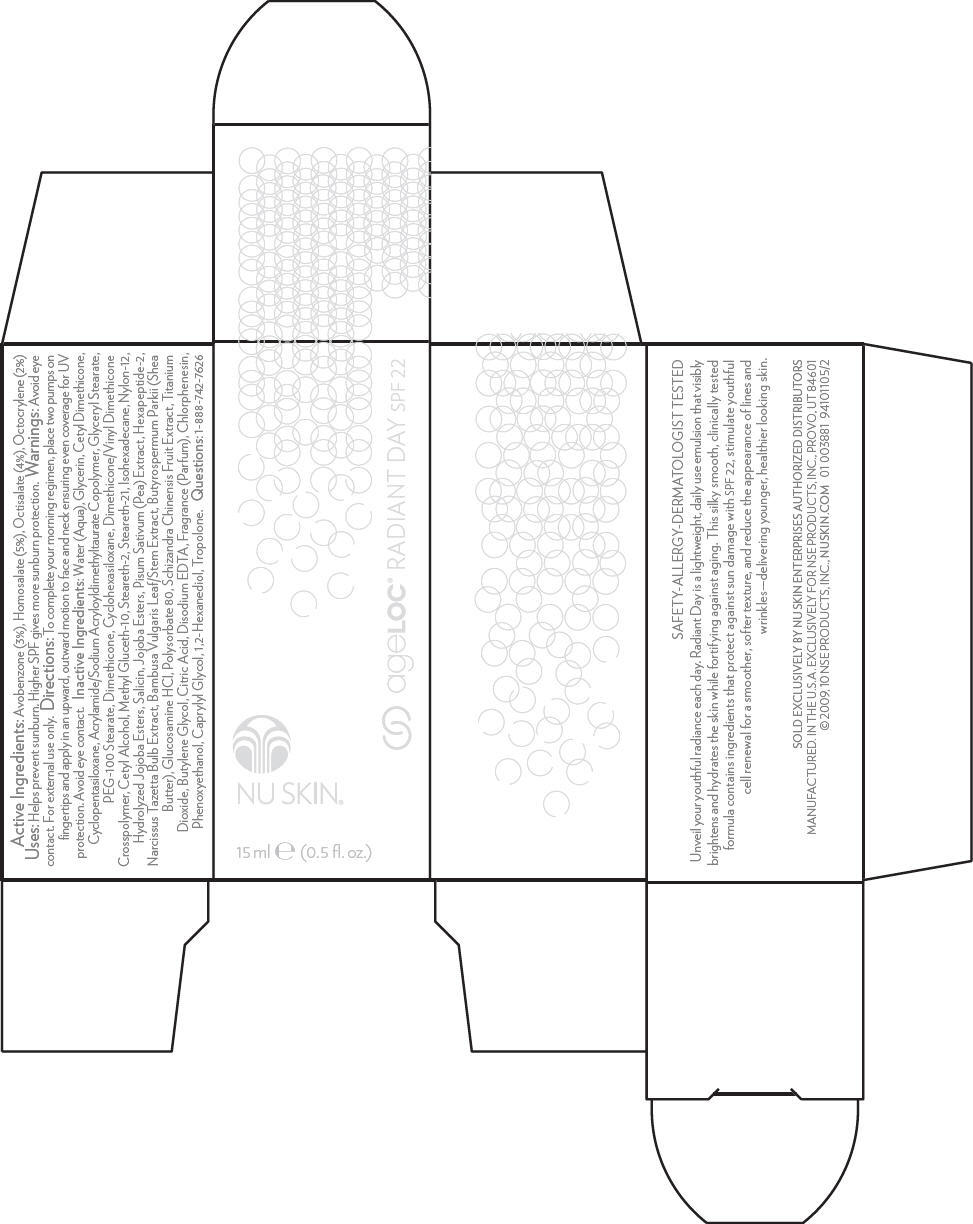 DRUG LABEL: NU SKIN
NDC: 62839-0289 | Form: LOTION
Manufacturer: NSE Products, Inc.
Category: otc | Type: HUMAN OTC DRUG LABEL
Date: 20100813

ACTIVE INGREDIENTS: Avobenzone 3 mL/100 mL; Homosalate 5 mL/100 mL; Octisalate 4 mL/100 mL; Octocrylene 2 mL/100 mL
INACTIVE INGREDIENTS: Water; Glycerin; Cyclomethicone 5; Glyceryl Monostearate; Polyoxyl 100 Stearate; Dimethicone; Cyclomethicone 6; Cetyl Alcohol; Methyl Gluceth-10; Steareth-2; Steareth-21; Isohexadecane; Hydrolyzed Jojoba Esters (Acid Form); Salicin; Bambusa Vulgaris Top; Shea Butter; Glucosamine Hydrochloride; Polysorbate 80; Titanium Dioxide; Butylene Glycol; Citric Acid Monohydrate; Edetate Disodium; Chlorphenesin; Phenoxyethanol; Caprylyl Glycol; Tropolone; 1,2-Hexanediol; Schisandra Chinensis Fruit

NU SKIN®
ageLOC® RADIANT DAY SPF 22

Active Ingredients

Avobenzone (3%), Homosalate (5%), Octisalate (4%), Octocrylene (2%)

Uses

Helps prevent sunburn. Higher SPF gives more sunburn protection.

Warnings

WHEN USING

Avoid eye contact. For external use only.

Directions

To complete your morning regimen, place two pumps on fingertips and apply in an upward, outward motion to face and neck ensuring even coverage for UV protection. Avoid eye contact.

Inactive Ingredients

Water (Aqua), Glycerin, Cetyl Dimethicone, Cyclopentasiloxane, Acrylamide/Sodium Acryloyldimethyltaurate Copolymer, Glyceryl Stearate, PEG-100 Stearate, Dimethicone, Cyclohexasiloxane, Dimethicone/Vinyl Dimethicone Crosspolymer, Cetyl Alcohol, Methyl Gluceth-10, Steareth-2, Steareth-21, Isohexadecane, Nylon-12, Hydrolyzed Jojoba Esters, Salicin, Jojoba Esters, Pisum Sativum (Pea) Extract, Hexapeptide-2, Narcissus Tazetta Bulb Extract, Bambusa Vulgaris Leaf/Stem Extract, Butyrospermum Parkii (Shea Butter), Glucosamine HCl, Polysorbate 80, Schizandra Chinensis Fruit Extract, Titanium Dioxide, Butylene Glycol, Citric Acid, Disodium EDTA, Fragrance (Parfum), Chlorphenesin, Phenoxyethanol, Caprylyl Glycol, 1,2-Hexanediol, Tropolone.

Questions

1-888-742-7626

PRINCIPAL DISPLAY PANEL - 15 ml Carton

NU SKIN®

15 ml e (0.5 fl. oz.)

ageLOC® RADIANT DAY SPF 22